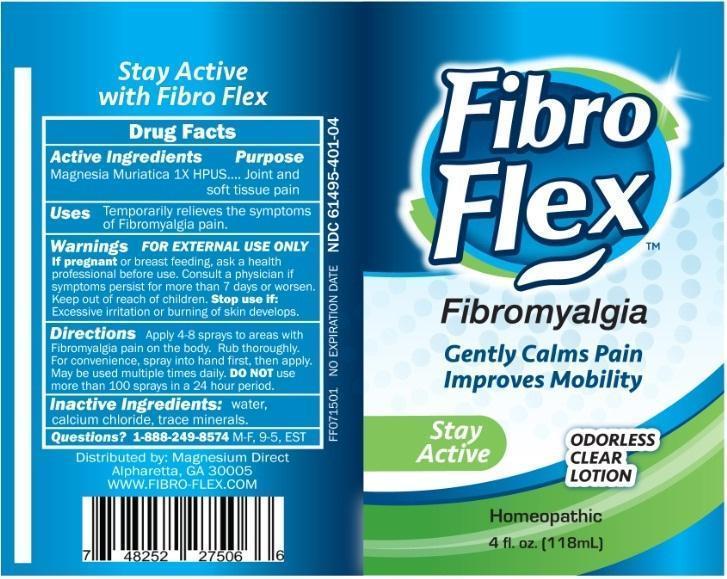 DRUG LABEL: Fibro Flex
NDC: 61495-401 | Form: SPRAY
Manufacturer: MAGNESIUM DIRECT INC.
Category: homeopathic | Type: HUMAN OTC DRUG LABEL
Date: 20150711

ACTIVE INGREDIENTS: MAGNESIUM CHLORIDE 1 [hp_X]/1 mL
INACTIVE INGREDIENTS: WATER; CALCIUM CHLORIDE

Fibro Flex

Active Ingredients

Magnesia Muriatica 1X HPUS

Purpose

Joint and soft tissue pain

Keep out of reach of children.

INDICATIONS AND USAGE

Uses Temporarily relieves the symptoms of Fibromyalgia pain.

Warnings FOR EXTERNAL USE ONLY

If pregnant or breast feeding, ask a health professional before use. Consult a physician if symptoms persist for more than 7 days or worsen. Stop use if: Excessive irritation or burning of skin develops.

DOSAGE AND ADMINISTRATION

Directions Apply 4-8 sprays to areas with Fibromyalgia pain on the body. Rub thoroughly. For convenience, spray into hand first, then apply. May be used multiple times daily. DO NOT use more than 100 sprays in a 24 hour period.

Inactive Ingredients: water, calcium chloride, trace minerals.

QUESTIONS

Questions? 1-888-249-8574 M-F, 9-5, EST

Distributed by: Magnesium Direct

Alpharetta, GA 30005

WWW. FIBRO-FLEX.COM